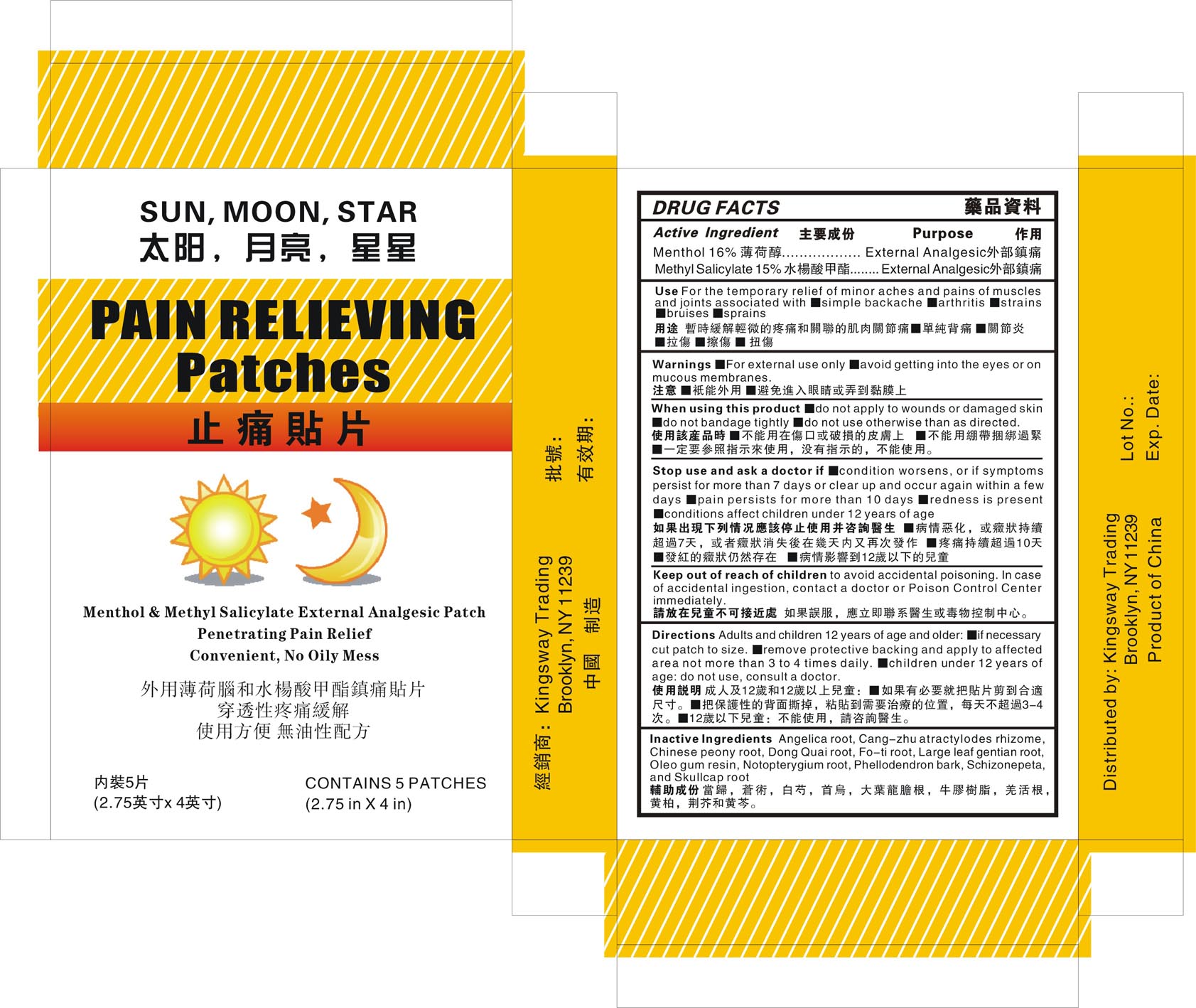 DRUG LABEL: Sun Moon Star 
NDC: 63922-222 | Form: PATCH
Manufacturer: Kingsway Trading
Category: otc | Type: HUMAN OTC DRUG LABEL
Date: 20110713

ACTIVE INGREDIENTS: Menthol 16 g/1 1; Methyl Salicylate 15 g/1 1
INACTIVE INGREDIENTS: ANGELICA ARCHANGELICA ROOT; ATRACTYLODES LANCEA ROOT; ANGELICA SINENSIS ROOT; GENTIANA MACROPHYLLA ROOT; NOTOPTERYGIUM FRANCHETII ROOT; PHELLODENDRON CHINENSIS BARK

Drug Facts

Active Ingredients

Menthol 16%
Methyl Salicylate 15%

Purpose

External Analgesic

Uses

For the temporary relief of minor pains and aches of muscles and joints associated with:

- simple backache
- arthritis
- strains
- bruises
- sprains

Warnings

- For external use only
- avoid getting into the eyes or on mucus membranes.

When using this product

- do not apply to wound or damaged skin.
- do not bandage tightly
- do not use otherwise than as directed

Stop use and ask a doctor if

- If condition worsens, or if symptoms persist for more than 7 days or clear up and occur again within a few days.
- pain persists for more than 10 days
- redness is present
- conditions affect children under 12 years of age

Keep out of reach of children to avoid accidental poisoning. In case of accidental ingestion, contact a doctor or Poison Control Center immediately

Directions
Adults and children 12 years of age and older:

- if necessary cut patch to size
- remove protective backing and apply to affected area not more than 3 to 4 times daily
- children under 12 years of age:do not use, consult a doctor

INACTIVE INGREDIENT

Inactive Ingredients Angelica root, Cang-zhu atractylodes rhizome, Chinese peony root, Dong Quai root, Fo-ti root, Large leaf gentian root, Oleo gum resin, Notopterygium root, Phellodendron bark, Schizonepeta, and Skullcap root

Package Label